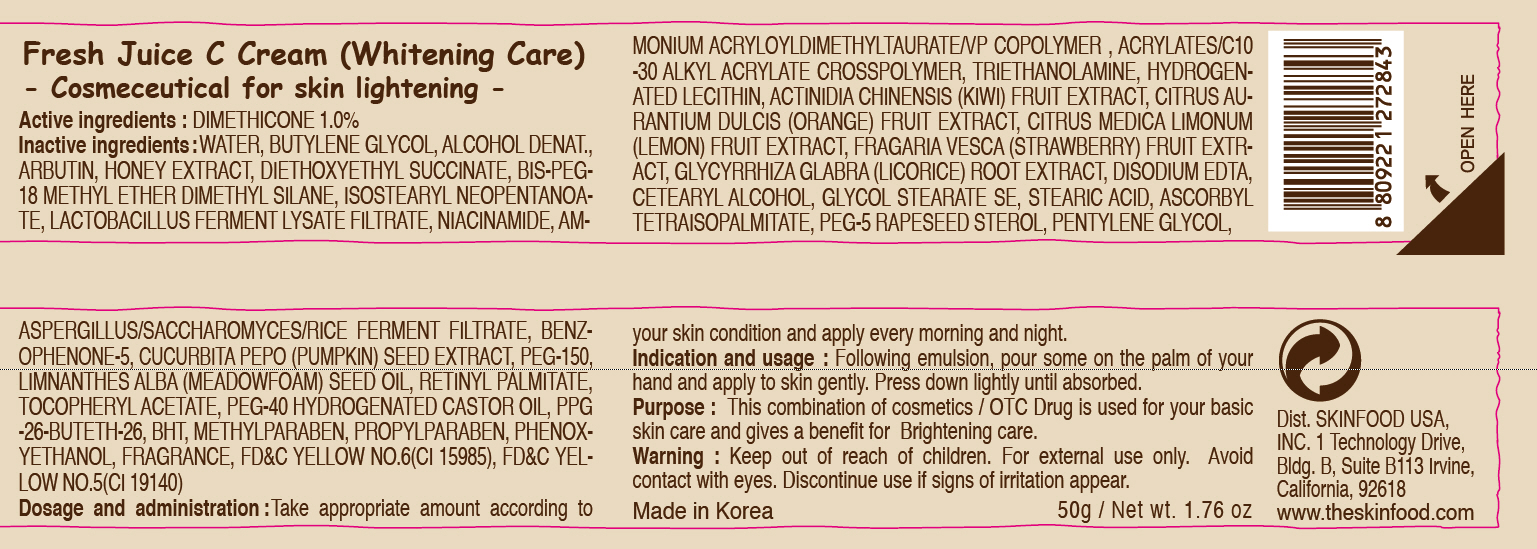 DRUG LABEL: FRESH JUICE C
NDC: 76214-023 | Form: CREAM
Manufacturer: SKINFOOD CO., LTD.
Category: otc | Type: HUMAN OTC DRUG LABEL
Date: 20110922

ACTIVE INGREDIENTS: DIMETHICONE 0.5 g/50 g
INACTIVE INGREDIENTS: WATER; BUTYLENE GLYCOL; ARBUTIN; HONEY; NIACINAMIDE; PHENOXYETHANOL; METHYLPARABEN; TROLAMINE; HYDROGENATED SOYBEAN LECITHIN; KIWI FRUIT; ORANGE; LEMON; GLYCYRRHIZA GLABRA; EDETATE DISODIUM; CETOSTEARYL ALCOHOL; STEARIC ACID; POLYETHYLENE GLYCOL 7000; PENTYLENE GLYCOL; BUTYLATED HYDROXYTOLUENE; PUMPKIN SEED; PROPYLPARABEN; MEADOWFOAM SEED OIL; VITAMIN A PALMITATE; POLYOXYL 40 HYDROGENATED CASTOR OIL

Drug Facts

Active ingredient: DIMETHICONE 1%

Inactive ingredients:
WATER, BUTYLENE GLYCOL, ALCOHOL DENAT., ARBUTIN, HONEY EXTRACT, DIETHOXYETHYL SUCCINATE, BIS-PEG-18 METHYL ETHER DIMETHYL SILANE, ISOSTEARYL NEOPENTANOATE, LACTOBACILLUS FERMENT LYSATE FILTRATE, NIACINAMIDE, AMMONIUM ACRYLOYLDIMETHYLTAURATE/VP COPOLYMER , ACRYLATES/C10-30 ALKYL ACRYLATE CROSSPOLYMER, TRIETHANOLAMINE, HYDROGENATED LECITHIN, ACTINIDIA CHINENSIS (KIWI) FRUIT EXTRACT, CITRUS AURANTIUM DULCIS (ORANGE) FRUIT EXTRACT, CITRUS MEDICA LIMONUM (LEMON) FRUIT EXTRACT, FRAGARIA VESCA (STRAWBERRY) FRUIT EXTRACT, GLYCYRRHIZA GLABRA (LICORICE) ROOT EXTRACT, DISODIUM EDTA, CETEARYL ALCOHOL, GLYCOL STEARATE SE, STEARIC ACID, ASCORBYL TETRAISOPALMITATE, PEG-5 RAPESEED STEROL, PENTYLENE GLYCOL, ASPERGILLUS/SACCHAROMYCES/RICE FERMENT FILTRATE, BENZOPHENONE-5, CUCURBITA PEPO (PUMPKIN) SEED EXTRACT, PEG-150, LIMNANTHES ALBA (MEADOWFOAM) SEED OIL, RETINYL PALMITATE, TOCOPHERYL ACETATE, PEG-40 HYDROGENATED CASTOR OIL, PPG-26-BUTETH-26, BHT, METHYLPARABEN, PROPYLPARABEN, PHENOXYETHANOL, FRAGRANCE

PURPOSE

Purpose: This combination of cosmetics / OTC Drug is used for your basic skin care and gives a benefit for Brightening care.

Warnings:
For external use only.
Avoid contact with eyes.
Discontinue use if signs of irritation appear.

Keep out of reach of children:
Keep out of reach of children.

Indication and usage:
Following emulsion, pour some on the palm of your hand and apply to skin gently.
Press down lightly until absorbed.

Dosage and administration:
Take appropriate amount according to your skin condition and apply every morning and night.